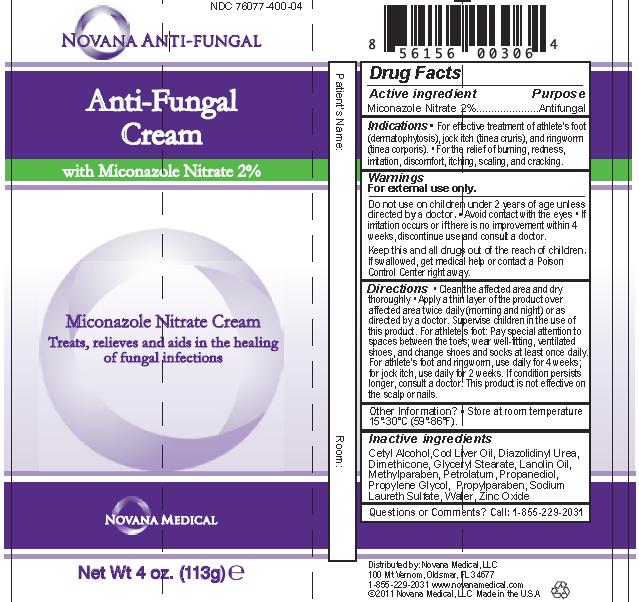 DRUG LABEL: Novana Antifungal Barrier with Miconazole
NDC: 76077-400 | Form: CREAM
Manufacturer: Novana Medical, LLC
Category: otc | Type: HUMAN OTC DRUG LABEL
Date: 20120404

ACTIVE INGREDIENTS: Miconazole Nitrate .02 mL/1 mL
INACTIVE INGREDIENTS: Water; Cetyl Alcohol; GLYCERYL MONOSTEARATE; Petrolatum; Lanolin; Cod Liver Oil; Propanediol; Sodium Laureth Sulfate; Propylene Glycol; Diazolidinyl Urea; Methylparaben; Propylparaben; Zinc Oxide; Dimethicone

Drug Facts

Active ingredient Purpose
Miconazole Nitrate 2%..............Antifungal

PURPOSE

Indications •For effective treatment of athlete's foot (dermatophytosis), jock itch (tinea cruris), and ringworm (tinea corporis). • For the relief of burning, redness, irritation, discomfort, itching, scaling, and cracking.

Warnings

For external use only.

Do not use on children under 2 years of age unless directed by a doctor. • Avoid contact with the eyes • If irritation occurs or if there is no improvement within 4 weeks, discontinue use and consult a doctor.

KEEP OUT OF REACH OF CHILDREN

Keep this and all drugs out of the reach of children. If swallowed, get medical help or contact a Poison Control Center right away.

INDICATIONS AND USAGE

Directions • Clean the affected area and dry thoroughly • Apply a thin layer of the product over affected area twice daily (morning and night) or as directed by a doctor. Supervise children in the use of this product. For athlete's foot: Pay special attention to spaces between the toes; wear well-fitting, ventilated shoes, and change shoes and socks at least once daily. For athlete's foot and ringworm, use daily for 4 weeks; for jock itch, use daily for 2 weeks. If condition persists longer, consult a doctor. This product is not effective on the scalp or nails.

DOSAGE AND ADMINISTRATION

Use Daily for 2 weeks.
If condition persists, consult a doctor. This product is not effective on scalp or nails.

Inactive ingredients
Cetyl Alcohol,Cod Liver Oil, Diazolidinyl Urea, Dimethicone, Glyceryl Stearate, Lanolin Oil, Methylparaben, Petrolatum, Propanediol, Propylene Glycol, Propylparaben, Sodium Laureth Sulfate, Water, Zinc Oxide